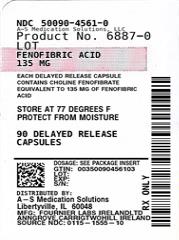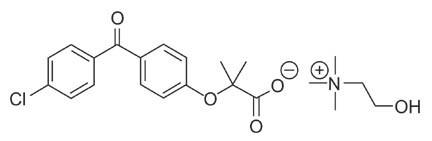 DRUG LABEL: Fenofibric Acid
NDC: 50090-4561 | Form: CAPSULE, DELAYED RELEASE
Manufacturer: A-S Medication Solutions
Category: prescription | Type: HUMAN PRESCRIPTION DRUG LABEL
Date: 20210415

ACTIVE INGREDIENTS: FENOFIBRIC ACID 135  mg/1 1
INACTIVE INGREDIENTS: HYPROMELLOSE, UNSPECIFIED

HIGHLIGHTS OF PRESCRIBING INFORMATION

These highlights do not include all the information needed to use fenofibric acid delayed release capsules safely and effectively. See full prescribing information for fenofibric acid delayed release capsules.
Fenofibric acid capsule, delayed release for oral use
Initial U.S. Approval: 2008

RECENT MAJOR CHANGES

Warnings and Precautions, Hypersensitivity Reactions (5.9) | 05/2018

1 INDICATIONS AND USAGE

Fenofibric acid delayed release capsules are a peroxisome proliferator-activated receptor (PPAR) alpha agonist indicated as adjunctive therapy to diet to:

- Reduce TG in patients with severe hypertriglyceridemia (1.1).
- Reduce elevated LDL-C, Total-C, TG and Apo B, and to increase HDL-C in patients with primary hypercholesterolemia or mixed dyslipidemia (1.2).

Limitations of Use: Fenofibrate at a dose equivalent to 135 mg of fenofibric acid delayed release capsules did not reduce coronary heart disease morbidity and mortality in patients with type 2 diabetes mellitus (5.1).

2 DOSAGE AND ADMINISTRATION

- Hypertriglyceridemia: 45 to 135 mg once daily (2.2).
- Primary hypercholesterolemia or mixed dyslipidemia: 135 mg once daily (2.3).
- Renally impaired patients: 45 mg once daily (2.4).
- Maximum dose: 135 mg once daily (2.1).
- May be taken without regard to food (2.1).

3 DOSAGE FORMS AND STRENGTHS

Oral Delayed Release Capsules: 45 mg and 135 mg (3).

4 CONTRAINDICATIONS

- Severe renal dysfunction, including patients receiving dialysis (4, 12.3).
- Active liver disease (4, 5.3).
- Gallbladder disease (4, 5.5).
- Nursing mothers (4, 8.2).
- Known hypersensitivity to fenofibric acid or fenofibrate (4, 5.9).

5 WARNINGS AND PRECAUTIONS

- Myopathy and rhabdomyolysis have been reported in patients taking fenofibrate. Risks are increased in elderly patients and patients with diabetes, renal failure, hypothyroidism, or statin co-administration (5.2).
- Fenofibric acid delayed release capsules can increase serum transaminases. Liver tests should be monitored periodically (5.3).
- Fenofibric acid delayed release capsules can reversibly increase serum creatinine levels (5.4). Monitor renal function periodically in patients with renal insufficiency (8.6).
- Fenofibric acid delayed release capsules increase cholesterol excretion into the bile, leading to risk of cholelithiasis. If suspected, gallbladder studies are indicated (5.5).
- Use caution in concomitant treatment with oral coumarin anticoagulants. Adjust the dosage of coumarin anticoagulant to maintain the prothrombin time/INR at the desired level to prevent bleeding complications (5.6).
- Acute hypersensitivity reactions, including anaphylaxis and angioedema, and delayed hypersensitivity reactions, including severe cutaneous adverse drug reactions have been reported postmarketing. Some cases were life-threatening and required emergency treatment. Discontinue fenofibrate and treat patients appropriately if reactions occur (5.9).

6 ADVERSE REACTIONS

The most common adverse events reported during clinical trials with fenofibrate (≥ 2% and at least 1% greater than placebo) were abnormal liver tests, increased AST, increased ALT, increased CPK, and rhinitis (6.1).
To report SUSPECTED ADVERSE REACTIONS, contact Amneal Pharmaceuticals at 1-877-835-5472 or FDA at 1-800-FDA-1088 or www.fda.gov/medwatch.

7 DRUG INTERACTIONS

- Coumarin Anticoagulants: (7.1).
- Bile Acid Binding Resins: (7.2).
- Immunosuppressants: (7.3).

8 USE IN SPECIFIC POPULATIONS

- Geriatric Use: Dose selection should be made based on renal function (8.5).
- Renal Impairment: Avoid use in severe renal impairment patients. Dose adjustment is required in mild to moderate renal impairment patients (8.6).

FULL PRESCRIBING INFORMATION

1 INDICATIONS AND USAGE

1.1 Treatment of Severe Hypertriglyceridemia

Fenofibric acid delayed release capsules are indicated as adjunctive therapy to diet to reduce triglycerides (TG) in patients with severe hypertriglyceridemia. Improving glycemic control in diabetic patients showing fasting chylomicronemia will usually obviate the need for pharmacological intervention. Markedly elevated levels of serum triglycerides (e.g. > 2,000 mg/dL) may increase the risk of developing pancreatitis. The effect of fenofibric acid delayed release capsules therapy on reducing this risk has not been adequately studied.

1.2 Treatment of Primary Hypercholesterolemia or Mixed Dyslipidemia

Fenofibric acid delayed release capsules are indicated as adjunctive therapy to diet to reduce elevated low-density lipoprotein cholesterol (LDL-C), total cholesterol (Total-C), triglycerides (TG), and apolipoprotein B (Apo B), and to increase high-density lipoprotein cholesterol (HDL-C) in patients with primary hypercholesterolemia or mixed dyslipidemia.

1.3 Limitations of Use

Fenofibrate at a dose equivalent to 135 mg of fenofibric acid delayed release capsules did not reduce coronary heart disease morbidity and mortality in 2 large, randomized controlled trials of patients with type 2 diabetes mellitus [see Warnings and Precautions (5.1)].

1.4 General Considerations for Treatment

Laboratory studies should be performed to establish that lipid levels are abnormal before instituting fenofibric acid delayed release capsules therapy.

Every reasonable attempt should be made to control serum lipids with non-drug methods including appropriate diet, exercise, weight loss in obese patients, and control of any medical problems such as diabetes mellitus and hypothyroidism that may be contributing to the lipid abnormalities. Medications known to exacerbate hypertriglyceridemia (beta-blockers, thiazides, estrogens) should be discontinued or changed if possible, and excessive alcohol intake should be addressed before triglyceride-lowering drug therapy is considered. If the decision is made to use lipid-altering drugs, the patient should be instructed that this does not reduce the importance of adhering to diet.

Drug therapy is not indicated for patients who have elevations of chylomicrons and plasma triglycerides, but who have normal levels of VLDL.

2 DOSAGE AND ADMINISTRATION

2.1 General Considerations

Patients should be placed on an appropriate lipid-lowering diet before receiving fenofibric acid delayed release capsules and should continue this diet during treatment. Fenofibric acid delayed release capsules can be taken without regard to meals. Patients should be advised to swallow fenofibric acid delayed release capsules whole. Do not open, crush, dissolve, or chew capsules. Serum lipids should be monitored periodically.

2.2 Severe Hypertriglyceridemia

The initial dose of fenofibric acid delayed release capsules is 45 to 135 mg once daily. Dosage should be individualized according to patient response, and should be adjusted if necessary following repeat lipid determinations at 4 to 8 week intervals. The maximum dose is 135 mg once daily.

2.3 Primary Hypercholesterolemia or Mixed Dyslipidemia

The dose of fenofibric acid delayed release capsules is 135 mg once daily.

2.4 Impaired Renal Function

Treatment with fenofibric acid delayed release capsules should be initiated at a dose of 45 mg once daily in patients with mild to moderate renal impairment and should only be increased after evaluation of the effects on renal function and lipid levels at this dose. The use of fenofibric acid delayed release capsules should be avoided in patients with severely impaired renal function [see Use in Specific Populations (8.6) and Clinical Pharmacology (12.3)].

2.5 Geriatric Patients

Dose selection for the elderly should be made on the basis of renal function [see Use in Specific Populations (8.5)].

3 DOSAGE FORMS AND STRENGTHS

- 45 mg capsules with a reddish brown to orange brown cap and a yellow body imprinted in black ink the number “45”.
- 45 mg capsules with a reddish brown to orange brown cap imprinted in white ink the “a” logo and a yellow body imprinted in black ink the number “45”.
- 135 mg capsules with a blue cap and a yellow body imprinted in black ink the number “135”.
- 135 mg capsules with a blue cap imprinted in white ink the “a” logo and a yellow body imprinted in black ink the number “135”.

4 CONTRAINDICATIONS

Fenofibric acid delayed release capsules are contraindicated in:

- patients with severe renal impairment, including those receiving dialysis [see Clinical Pharmacology (12.3)].
- patients with active liver disease, including those with primary biliary cirrhosis and unexplained persistent liver function abnormalities [see Warnings and Precautions (5.3)].
- patients with preexisting gallbladder disease [see Warnings and Precautions (5.5)].
- nursing mothers [see Use in Specific Populations (8.2)].
- patients with hypersensitivity to fenofibric acid or fenofibrate [see Warnings and Precautions (5.9)].

5 WARNINGS AND PRECAUTIONS

5.1 Mortality and Coronary Heart Disease Morbidity

The effect of fenofibric acid delayed release capsules on coronary heart disease morbidity and mortality and non-cardiovascular mortality has not been established. Because of similarities between fenofibric acid delayed release capsules and fenofibrate, clofibrate, and gemfibrozil, the findings in the following large randomized, placebo-controlled clinical studies with these fibrate drugs may also apply to fenofibric acid delayed release capsules.

The Action to Control Cardiovascular Risk in Diabetes Lipid (ACCORD Lipid) trial was a randomized placebo-controlled study of 5518 patients with type 2 diabetes mellitus on background statin therapy treated with fenofibrate. The mean duration of follow-up was 4.7 years. Fenofibrate plus statin combination therapy showed a non-significant 8% relative risk reduction in the primary outcome of major adverse cardiovascular events (MACE), a composite of non-fatal myocardial infarction, non-fatal stroke, and cardiovascular disease death (hazard ratio [HR] 0.92, 95% CI 0.79-1.08) (p=0.32) as compared to statin monotherapy. In a gender subgroup analysis, the hazard ratio for MACE in men receiving combination therapy versus statin monotherapy was 0.82 (95% CI 0.69-0.99), and the hazard ratio for MACE in women receiving combination therapy versus statin monotherapy was 1.38 (95% CI 0.98-1.94) (interaction p=0.01). The clinical significance of this subgroup finding is unclear.

The Fenofibrate Intervention and Event Lowering in Diabetes (FIELD) study was a 5-year randomized, placebo-controlled study of 9795 patients with type 2 diabetes mellitus treated with fenofibrate. Fenofibrate demonstrated a non-significant 11% relative reduction in the primary outcome of coronary heart disease events (hazard ratio [HR] 0.89, 95% CI 0.75-1.05, p = 0.16) and a significant 11% reduction in the secondary outcome of total cardiovascular disease events (HR 0.89 [0.80-0.99], p = 0.04). There was a non-significant 11% (HR 1.11 [0.95, 1.29], p = 0.18) and 19% (HR 1.19 [0.90, 1.57], p = 0.22) increase in total and coronary heart disease mortality, respectively, with fenofibrate as compared to placebo.

In the Coronary Drug Project, a large study of post-myocardial infarction patients treated for 5 years with clofibrate, there was no difference in mortality seen between the clofibrate group and the placebo group. There was, however, a difference in the rate of cholelithiasis and cholecystitis requiring surgery between the two groups (3.0% vs. 1.8%).

In a study conducted by the World Health Organization (WHO), 5000 subjects without known coronary artery disease were treated with placebo or clofibrate for 5 years and followed for an additional one year. There was a statistically significant, higher age-adjusted all-cause mortality in the clofibrate group compared with the placebo group (5.70% vs. 3.96%, p = < 0.01). Excess mortality was due to a 33% increase in non-cardiovascular causes, including malignancy, post-cholecystectomy complications, and pancreatitis. This appeared to confirm the higher risk of gallbladder disease seen in clofibrate-treated patients studied in the Coronary Drug Project.

The Helsinki Heart Study was a large (N = 4081) study of middle-aged men without a history of coronary artery disease. Subjects received either placebo or gemfibrozil for 5 years, with a 3.5 year open extension afterward. Total mortality was numerically higher in the gemfibrozil randomization group but did not achieve statistical significance (p = 0.19, 95% confidence interval for relative risk G:P = 0.91-1.64). Although cancer deaths trended higher in the gemfibrozil group (p = 0.11), cancers (excluding basal cell carcinoma) were diagnosed with equal frequency in both study groups. Due to the limited size of the study, the relative risk of death from any cause was not shown to be different than that seen in the 9 year follow-up data from WHO study (RR = 1.29). A secondary prevention component of the Helsinki Heart Study enrolled middle-aged men excluded from the primary prevention study because of known or suspected coronary heart disease. Subjects received gemfibrozil or placebo for 5 years. Although cardiac deaths trended higher in the gemfibrozil group, this was not statistically significant (hazard ratio 2.2, 95% confidence interval: 0.94-5.05).

5.2 Skeletal Muscle

Fibrates increase the risk of myositis or myopathy and have been associated with rhabdomyolysis. The risk for serious muscle toxicity appears to be increased in elderly patients and in patients with diabetes, renal failure, or hypothyroidism.

Myopathy should be considered in any patient with diffuse myalgias, muscle tenderness or weakness, and/or marked elevations of CPK levels. Patients should promptly report unexplained muscle pain, tenderness or weakness, particularly if accompanied by malaise or fever. CPK levels should be assessed in patients reporting these symptoms, and fenofibric acid delayed release capsules should be discontinued if markedly elevated CPK levels occur or myopathy or myositis is suspected or diagnosed.

Data from observational studies suggest that the risk for rhabdomyolysis is increased when fibrates are co-administered with a statin.

Cases of myopathy, including rhabdomyolysis, have been reported with fenofibrates co-administered with colchicine, and caution should be exercised when prescribing fenofibrate with colchicine [see Drug Interactions (7.4)].

5.3 Liver Function

Fenofibric acid delayed release capsules at a dose of 135 mg once daily has been associated with increases in serum transaminases [AST (SGOT) or ALT (SGPT)]. In a pooled analysis of three 12‑week, double-blind, controlled studies of fenofibric acid delayed release capsules, increases in ALT and AST to > 3 times the upper limit of normal on two consecutive occasions occurred in 1.9% and 0.2%, respectively, of patients receiving fenofibric acid delayed release capsules without other lipid-altering drugs. Increases in ALT and/or AST were not accompanied by increases in bilirubin or clinically significant increases in alkaline phosphatase.

In a pooled analysis of 10 placebo-controlled trials of fenofibrate, increases to > 3 times the upper limit of normal in ALT occurred in 5.3% of patients taking fenofibrate versus 1.1% of patients treated with placebo. The incidence of increases in transaminases observed with fenofibrate therapy may be dose related. In an 8-week dose-ranging study of fenofibrate in hypertriglyceridemia, the incidence of ALT or AST elevations ≥ 3 times the upper limit of normal was 13% in patients receiving dosages equivalent to 90 mg to 135 mg fenofibric acid delayed release capsules once daily and was 0% in those receiving dosages equivalent to 45 mg fenofibric acid delayed release capsules once daily or less, or placebo. Hepatocellular, chronic active, and cholestatic hepatitis observed with fenofibrate therapy have been reported after exposures of weeks to several years. In extremely rare cases, cirrhosis has been reported in association with chronic active hepatitis.

Baseline and regular monitoring of liver function, including serum ALT (SGPT) should be performed for the duration of therapy with fenofibric acid delayed release capsules, and therapy discontinued if enzyme levels persist above 3 times the upper limit of normal.

5.4 Serum Creatinine

Reversible elevations in serum creatinine have been reported in patients receiving fenofibric acid delayed release capsules as well as patients receiving fenofibrate. In the pooled analysis of three 12‑week, double-blind, controlled studies of fenofibric acid delayed release capsules, increases in creatinine to > 2 mg/dL occurred in 0.8% of patients treated with fenofibric acid delayed release capsules without other lipid-altering drugs. Elevations in serum creatinine were generally stable over time with no evidence for continued increases in serum creatinine with long-term therapy and tended to return to baseline following discontinuation of treatment. The clinical significance of these observations is unknown. Monitoring renal function in patients with renal impairment taking fenofibric acid delayed release capsules is suggested. Renal monitoring should be considered for patients at risk for renal insufficiency, such as the elderly and those with diabetes.

5.5 Cholelithiasis

Fenofibric acid delayed release capsules, like fenofibrate, clofibrate, and gemfibrozil, may increase cholesterol excretion into the bile, potentially leading to cholelithiasis. If cholelithiasis is suspected, gallbladder studies are indicated. Fenofibric acid delayed release capsules therapy should be discontinued if gallstones are found.

5.6 Coumarin Anticoagulants

Caution should be exercised when fenofibric acid delayed release capsules are given in conjunction with oral coumarin anticoagulants. Fenofibric acid delayed release capsules may potentiate the anticoagulant effects of these agents resulting in prolongation of the prothrombin time/International Normalized Ratio (PT/INR). Frequent monitoring of PT/INR and dose adjustment of the oral anticoagulant are recommended until the PT/INR has stabilized in order to prevent bleeding complications [see Drug Interactions (7.1)].

5.7 Pancreatitis

Pancreatitis has been reported in patients taking drugs of the fibrate class, including fenofibric acid delayed release capsules. This occurrence may represent a failure of efficacy in patients with severe hypertriglyceridemia, a direct drug effect, or a secondary phenomenon mediated through biliary tract stone or sludge formation with obstruction of the common bile duct.

5.8 Hematological Changes

Mild to moderate hemoglobin, hematocrit, and white blood cell decreases have been observed in patients following initiation of fenofibric acid delayed release capsules and fenofibrate therapy. However, these levels stabilize during long-term administration. Thrombocytopenia and agranulocytosis have been reported in individuals treated with fenofibrates. Periodic monitoring of red and white blood cell counts are recommended during the first 12 months of fenofibric acid delayed release capsules administration.

5.9 Hypersensitivity Reactions

Acute Hypersensitivity

Anaphylaxis and angioedema have been reported postmarketing with fenofibrate. In some cases, reactions were life-threatening and required emergency treatment. If a patient develops signs or symptoms of an acute hypersensitivity reaction, advise them to seek immediate medical attention and discontinue fenofibrate.

Delayed Hypersensitivity

Severe cutaneous adverse drug reactions (SCAR), including Stevens-Johnson syndrome, toxic epidermal necrolysis, and Drug Reaction with Eosinophilia and Systemic Symptoms (DRESS), have been reported postmarketing, occurring days to weeks after initiation of fenofibrate. The cases of DRESS were associated with cutaneous reactions (such as rash or exfoliative dermatitis) and a combination of eosinophilia, fever, systemic organ involvement (renal, hepatic, or respiratory). Discontinue fenofibrate and treat patients appropriately if SCAR is suspected.

5.10 Venothromboembolic Disease

In the FIELD trial, pulmonary embolus (PE) and deep vein thrombosis (DVT) were observed at higher rates in the fenofibrate- than the placebo-treated group. Of 9,795 patients enrolled in FIELD, there were 4,900 in the placebo group and 4,895 in the fenofibrate group. For DVT, there were 48 events (1%) in the placebo group and 67 (1%) in the fenofibrate group (p = 0.074); and for PE, there were 32 (0.7%) events in the placebo group and 53 (1%) in the fenofibrate group (p = 0.022).

In the Coronary Drug Project, a higher proportion of the clofibrate group experienced definite or suspected fatal or nonfatal PE or thrombophlebitis than the placebo group (5.2% vs. 3.3% at five years; p < 0.01).

5.11 Paradoxical Decreases in HDL Cholesterol Levels

There have been postmarketing and clinical trial reports of severe decreases in HDL cholesterol levels (as low as 2 mg/dL) occurring in diabetic and non-diabetic patients initiated on fibrate therapy. The decrease in HDL-C is mirrored by a decrease in apolipoprotein A1. This decrease has been reported to occur within 2 weeks to years after initiation of fibrate therapy. The HDL-C levels remain depressed until fibrate therapy has been withdrawn; the response to withdrawal of fibrate therapy is rapid and sustained. The clinical significance of this decrease in HDL-C is unknown. It is recommended that HDL-C levels be checked within the first few months after initiation of fibrate therapy. If a severely depressed HDL-C level is detected, fibrate therapy should be withdrawn, and the HDL-C level monitored until it has returned to baseline, and fibrate therapy should not be re-initiated.

6 ADVERSE REACTIONS

6.1 Clinical Trials Experience

Because clinical studies are conducted under widely varying conditions, adverse reaction rates observed in the clinical studies of a drug cannot be directly compared to rates in the clinical studies of another drug and may not reflect the rates observed in practice.

Fenofibric acid is the active metabolite of fenofibrate. Adverse events reported by 2% or more of patients treated with fenofibrate and greater than placebo during double-blind, placebo-controlled trials are listed in Table 1. Adverse events led to discontinuation of treatment in 5.0% of patients treated with fenofibrate and in 3.0% treated with placebo. Increases in liver tests were the most frequent events, causing discontinuation of fenofibrate treatment in 1.6% of patients in double-blind trials.

Table 1. Adverse Events Reported by 2% or More of Patients Treated with Fenofibrate and Greater than Placebo During the Double-Blind, Placebo-Controlled Trials
BODY SYSTEM Adverse Event | Fenofibrate* (N = 439) | Placebo (N = 365)
BODY AS A WHOLE
Abdominal Pain | 4.6% | 4.4%
Back Pain | 3.4% | 2.5%
Headache | 3.2% | 2.7%
DIGESTIVE
Nausea | 2.3% | 1.9%
Constipation | 2.1% | 1.4%
INVESTIGATIONS
Abnormal Liver Tests | 7.5% | 1.4%
Increased AST | 3.4% | 0.5%
Increased ALT | 3.0% | 1.6%
Increased Creatine Phosphokinase | 3.0% | 1.4%
RESPIRATORY
Respiratory Disorder | 6.2% | 5.5%
Rhinitis | 2.3% | 1.1%
* Dosage equivalent to 135 mg fenofibric acid delayed release capsules

Urticaria was seen in 1.1% vs. 0%, and rash in 1.4% vs. 0.8% of fenofibrate and placebo patients respectively in controlled trials.

Clinical trials with fenofibric acid delayed release capsules did not include a placebo-control arm. However, the adverse event profile of fenofibric acid delayed release capsules was generally consistent with that of fenofibrate. The following adverse events not listed above were reported in ≥ 3% of patients taking fenofibric acid delayed release capsules alone:

Gastrointestinal Disorders: Diarrhea, dyspepsia

General Disorders and Administration Site Conditions: Pain

Infections and Infestations: Nasopharyngitis, sinusitis, upper respiratory tract infection

Musculoskeletal and Connective Tissue Disorders: Arthralgia, myalgia, pain in extremity

Nervous System Disorders: Dizziness

6.2 Postmarketing Experience

The following adverse reactions have been identified during postapproval use of fenofibrate. Because these reactions are reported voluntarily from a population of uncertain size, it is not always possible to reliably estimate their frequency or establish a causal relationship to drug exposure: rhabdomyolysis, pancreatitis, renal failure, muscle spasms, acute renal failure, hepatitis, cirrhosis, anemia, asthenia, severely depressed HDL-cholesterol levels, and interstitial lung disease. Photosensitivity reactions to fenofibrate have occurred days to months after initiation; in some of these cases, patients reported a prior photosensitivity reaction to ketoprofen.

7 DRUG INTERACTIONS

7.1 Coumarin Anticoagulants

Potentiation of coumarin-type anticoagulant effect has been observed with prolongation of the PT/INR.

Caution should be exercised when oral coumarin anticoagulants are given in conjunction with fenofibric acid delayed release capsules. The dosage of the anticoagulant should be reduced to maintain the PT/INR at the desired level to prevent bleeding complications. Frequent PT/INR determinations are advisable until it has been definitely determined that the PT/INR has stabilized [see Warnings and Precautions (5.6)].

7.2 Bile Acid Binding Resins

Since bile acid binding resins may bind other drugs given concurrently, patients should take fenofibric acid delayed release capsules at least 1 hour before or 4 to 6 hours after a bile acid resin to avoid impeding its absorption.

7.3 Immunosuppressants

Immunosuppressants such as cyclosporine and tacrolimus can produce nephrotoxicity with decreases in creatinine clearance and rises in serum creatinine, and because renal excretion is the primary elimination route of drugs of the fibrate class including fenofibric acid delayed release capsules, there is a risk that an interaction will lead to deterioration of renal function. The benefits and risks of using fenofibric acid delayed release capsules with immunosuppressants and other potentially nephrotoxic agents should be carefully considered, and the lowest effective dose employed.

7.4 Colchicine

Cases of myopathy, including rhabdomyolysis, have been reported with fenofibrates co-administered with colchicine, and caution should be exercised when prescribing fenofibrate with colchicine.

8 USE IN SPECIFIC POPULATIONS

8.1 Pregnancy

Risk Summary

Limited available data with fenofibrate use in pregnant women are insufficient to determine a drug associated risk of major birth defects, miscarriage or adverse maternal or fetal outcomes. In animal reproduction studies, no evidence of embryo-fetal toxicity was observed with oral administration of fenofibrate in rats and rabbits during organogenesis at doses less than or equivalent to the maximum recommended clinical dose of 135 mg daily, based on body surface area (mg/m^2). Adverse reproductive outcomes occurred at higher doses in the presence of maternal toxicity (see Data). Fenofibric acid delayed release capsules should be used during pregnancy only if the potential benefit justifies the potential risk to the fetus.

The estimated background risk of major birth defects and miscarriage for the indicated population is unknown. In the U.S. general population, the estimated background risk of major birth defects and miscarriage in clinically recognized pregnancies is 2-4% and 15-20%, respectively.

Data

Animal Data

In pregnant rats given oral dietary doses of 14, 127, and 361 mg/kg/day from gestation day 6-15 during the period of organogenesis, no adverse developmental findings were observed at 14 mg/kg/day (less than the clinical exposure at the maximum recommended human dose [MRHD] of 300 mg fenofibrate daily, equivalent to 135 mg fenofibric acid delayed release capsules daily, based on body surface area comparisons). Increased fetal skeletal malformations were observed at maternally toxic doses (361 mg/kg/day, corresponding to 12 times the clinical exposure at the MRHD) that significantly suppressed maternal body weight gain.

In pregnant rabbits given oral gavage doses of 15, 150, and 300 mg/kg/day from gestation day 6-18 during the period of organogenesis and allowed to deliver, no adverse developmental findings were observed at 15 mg/kg/day (a dose that approximates the clinical exposure at the MRHD, based on body surface area comparisons). Aborted litters were observed at maternally toxic doses (≥ 150 mg/kg/day, corresponding to ≥ 10 times the clinical exposure at the MRHD) that suppressed maternal body weight gain.

In pregnant rats given oral dietary doses of 15, 75, and 300 mg/kg/day from gestation day 15 through lactation day 21 (weaning), no adverse developmental effects were observed at 15 mg/kg/day (less than the clinical exposure at the MRHD, based on body surface area comparisons), despite maternal toxicity (decreased weight gain). Post-implantation loss was observed at ≥ 75 mg/kg/day (≥ 2 times the clinical exposure at the MRHD) in the presence of maternal toxicity (decreased weight gain). Decreased pup survival was noted at 300 mg/kg/day (10 times the clinical exposure at the MRHD), which was associated with decreased maternal body weight gain/maternal neglect.

8.2 Lactation

Risk Summary

There is no available information on the presence of fenofibrate in human milk, effects of the drug on the breastfed infant, or the effects on milk production. Fenofibrate is present in the milk of rats, and is therefore likely to be present in human milk. Because of the potential for serious adverse reactions in breastfed infants, such as disruption of infant lipid metabolism, women should not breastfeed during treatment with fenofibric acid delayed release capsules and for 5 days after the final dose [see Contraindications (4)].

8.4 Pediatric Use

The safety and effectiveness of fenofibric acid delayed release capsules in pediatric patients have not been established.

8.5 Geriatric Use

Fenofibric acid delayed release capsules are substantially excreted by the kidney as fenofibric acid and fenofibric acid glucuronide, and the risk of adverse reactions to this drug may be greater in patients with impaired renal function. Fenofibric acid exposure is not influenced by age. Since elderly patients have a higher incidence of renal impairment, dose selection for the elderly should be made on the basis of renal function [see Dosage and Administration (2.5) and Clinical Pharmacology (12.3)]. Elderly patients with normal renal function should require no dose modifications. Consider monitoring renal function in elderly patients taking fenofibric acid delayed release capsules.

8.6 Renal Impairment

The use of fenofibric acid delayed release capsules should be avoided in patients who have severe renal impairment [see Contraindications (4)]. Dose reduction is required in patients with mild to moderate renal impairment [see Dosage and Administration (2.4) and Clinical Pharmacology (12.3)]. Monitoring renal function in patients with renal impairment is recommended.

8.7 Hepatic Impairment

The use of fenofibric acid delayed release capsules has not been evaluated in subjects with hepatic impairment [see Contraindications (4) and Clinical Pharmacology (12.3)].

10 OVERDOSAGE

There is no specific treatment for overdose with fenofibric acid delayed release capsules. General supportive care of the patient is indicated, including monitoring of vital signs and observation of clinical status, should an overdose occur. If indicated, elimination of unabsorbed drug should be achieved by emesis or gastric lavage; usual precautions should be observed to maintain the airway. Because fenofibric acid delayed release capsules are highly bound to plasma proteins, hemodialysis should not be considered.

11 DESCRIPTION

Fenofibric acid delayed release capsules (fenofibric acid) are a lipid regulating agent available as delayed release capsules for oral administration. Each delayed release capsule contains choline fenofibrate, equivalent to 45 mg or 135 mg of fenofibric acid. The chemical name for choline fenofibrate is ethanaminium, 2-hydroxy-N,N,N-trimethyl, 2-{4-(4-chlorobenzoyl)phenoxy] -2-methylpropanoate (1:1) with the following structural formula:

The empirical formula is C22H28ClNO5 and the molecular weight is 421.91. Choline fenofibrate is freely soluble in water. The melting point is approximately 210°C. Choline fenofibrate is a white to yellow powder, which is stable under ordinary conditions.

Each delayed release capsule contains enteric coated mini-tablets comprised of choline fenofibrate and the following inactive ingredients: hypromellose, povidone, water, hydroxypropyl cellulose, colloidal silicon dioxide, sodium stearyl fumarate, methacrylic acid copolymer, talc, triethyl citrate. The capsule shell of the 45 mg capsule contains the following inactive ingredients: gelatin, titanium dioxide, yellow iron oxide, black iron oxide, and red iron oxide. The capsule shell of the 135 mg capsule contains the following inactive ingredients: gelatin, titanium dioxide, yellow iron oxide, and FD&C Blue #2.

12 CLINICAL PHARMACOLOGY

12.1 Mechanism of Action

The active moiety of fenofibric acid delayed release capsules is fenofibric acid. The pharmacological effects of fenofibric acid in both animals and humans have been extensively studied through oral administration of fenofibrate.

The lipid-modifying effects of fenofibric acid seen in clinical practice have been explained in vivo in transgenic mice and in vitro in human hepatocyte cultures by the activation of peroxisome proliferator activated receptor α (PPARα). Through this mechanism, fenofibric acid increases lipolysis and elimination of triglyceride-rich particles from plasma by activating lipoprotein lipase and reducing production of Apo CIII (an inhibitor of lipoprotein lipase activity).

Activation of PPARα also induces an increase in the synthesis of HDL-C and Apo AI and AII.

12.3 Pharmacokinetics

Fenofibric acid delayed release capsules contain fenofibric acid, which is the only circulating pharmacologically active moiety in plasma after oral administration of fenofibric acid delayed release capsules. Fenofibric acid is also the circulating pharmacologically active moiety in plasma after oral administration of fenofibrate, the ester of fenofibric acid.

Plasma concentrations of fenofibric acid after administration of one 135 mg fenofibric acid delayed release capsule are equivalent to those after one 200 mg capsule of micronized fenofibrate administered under fed conditions.

Absorption
Fenofibric acid is well absorbed throughout the gastrointestinal tract. The absolute bioavailability of fenofibric acid is approximately 81%.

Peak plasma levels of fenofibric acid occur within 4 to 5 hours after a single dose administration of fenofibric acid delayed release capsules under fasting conditions.

Fenofibric acid exposure in plasma, as measured by Cmax and AUC, is not significantly different when a single 135 mg dose of fenofibric acid delayed release capsules is administered under fasting or nonfasting conditions.

Distribution
Upon multiple dosing of fenofibric acid delayed release capsules, fenofibric acid levels reach steady state within 8 days. Plasma concentrations of fenofibric acid at steady state are approximately slightly more than double those following a single dose. Serum protein binding is approximately 99% in normal and dyslipidemic subjects.

Metabolism
Fenofibric acid is primarily conjugated with glucuronic acid and then excreted in urine. A small amount of fenofibric acid is reduced at the carbonyl moiety to a benzhydrol metabolite which is, in turn, conjugated with glucuronic acid and excreted in urine.

In vivo metabolism data after fenofibrate administration indicate that fenofibric acid does not undergo oxidative metabolism (e.g., cytochrome P450) to a significant extent.

Elimination
After absorption, fenofibric acid delayed release capsules are primarily excreted in the urine in the form of fenofibric acid and fenofibric acid glucuronide.

Fenofibric acid is eliminated with a half-life of approximately 20 hours, allowing once daily administration of fenofibric acid delayed release capsules.

Specific Populations
Geriatrics
In five elderly volunteers 77 to 87 years of age, the oral clearance of fenofibric acid following a single oral dose of fenofibrate was 1.2 L/h, which compares to 1.1 L/h in young adults. This indicates that an equivalent dose of fenofibric acid delayed release capsules can be used in elderly subjects with normal renal function, without increasing accumulation of the drug or metabolites [see Use in Specific Populations (8.5)].

Pediatrics
The pharmacokinetics of fenofibric acid delayed release capsules has not been studied in pediatric populations.

Gender
No pharmacokinetic difference between males and females has been observed for fenofibric acid delayed release capsules.

Race
The influence of race on the pharmacokinetics of fenofibric acid delayed release capsules has not been studied; however, fenofibric acid is not metabolized by enzymes known for exhibiting inter-ethnic variability.

Renal Impairment
The pharmacokinetics of fenofibric acid was examined in patients with mild, moderate, and severe renal impairment. Patients with severe renal impairment (estimated glomerular filtration rate [eGFR] <30 mL/min/1.73m^2) showed a 2.7-fold increase in exposure for fenofibric acid and increased accumulation of fenofibric acid during chronic dosing compared to that of healthy subjects. Patients with mild to moderate renal impairment (eGFR 30-59 mL/min/1.73m^2) had similar exposure but an increase in the half-life for fenofibric acid compared to that of healthy subjects. Based on these findings, the use of fenofibric acid delayed release capsules should be avoided in patients who have severe renal impairment and dose reduction is required in patients having mild to moderate renal impairment [see Dosage and Administration (2.4)].

Hepatic Impairment
No pharmacokinetic studies have been conducted in patients with hepatic impairment.

Drug-drug Interactions
In vitro studies using human liver microsomes indicate that fenofibric acid is not an inhibitor of cytochrome (CYP) P450 isoforms CYP3A4, CYP2D6, CYP2E1, or CYP1A2. It is a weak inhibitor of CYP2C8, CYP2C19, and CYP2A6, and mild-to-moderate inhibitor of CYP2C9 at therapeutic concentrations.

Comparison of atorvastatin exposures when atorvastatin (80 mg once daily for 10 days) is given in combination with fenofibric acid (fenofibric acid delayed release capsules 135 mg once daily for 10 days) and ezetimibe (10 mg once daily for 10 days) versus when atorvastatin is given in combination with ezetimibe only (ezetimibe 10 mg once daily and atorvastatin, 80 mg once daily for 10 days): The Cmax decreased by 1% for atorvastatin and ortho-hydroxy-atorvastatin and increased by 2% for parahydroxy-atorvastatin. The AUC decreased 6% and 9% for atorvastatin and orthohydroxy-atorvastatin, respectively, and did not change for para-hydroxy-atorvastatin.

Comparison of ezetimibe exposures when ezetimibe (10 mg once daily for 10 days) is given in combination with fenofibric acid (fenofibric acid delayed release capsules 135 mg once daily for 10 days) and atorvastatin (80 mg once daily for 10 days) versus when ezetimibe is given in combination with atorvastatin only (ezetimibe 10 mg once daily and atorvastatin, 80 mg once daily for 10 days): The Cmax increased by 26% and 7% for total and free ezetimibe, respectively. The AUC increased by 27% and 12% for total and free ezetimibe, respectively.

Table 2 describes the effects of co-administered drugs on fenofibric acid systemic exposure. Table 3 describes the effects of co-administered fenofibric acid on other drugs.

Table 2. Effects of Co-Administered Drugs on Fenofibric Acid Systemic Exposure from Fenofibric Acid Delayed Release Capsules or Fenofibrate Administration
Co- Administered Drug | Dosage Regimen of Co-Administered Drug | Dosage Regimen of Fenofibric Acid Delayed Release Capsules or Fenofibrate | Changes in Fenofibric Acid Exposure
 |  |  | AUC | Cmax
Lipid-lowering agents
Rosuvastatin | 40 mg once daily for 10 days | Fenofibric acid delayed release capsules 135 mg once daily for 10 days | ↓2% | ↓2%
Atorvastatin | 20 mg once daily for 10 days | Fenofibrate 160 mg^1 once daily for 10 days | ↓2% | ↓4%
Atorvastatin + ezetimibe | Atorvastatin, 80 mg once daily and ezetimibe, 10 mg once daily for 10 days | Fenofibric acid delayed release capsules 135 mg once daily for 10 days | ↑5% | ↑5%
Pravastatin | 40 mg as a single dose | Fenofibrate 3 x 67 mg^2 as a single dose | ↓1% | ↓2%
Fluvastatin | 40 mg as a single dose | Fenofibrate 160 mg^1 as a single dose | ↓2% | ↓10%
Simvastatin | 80 mg once daily for 7 days | Fenofibrate 160 mg^1 once daily for 7 days | ↓5% | ↓11%
Anti-diabetic agents
Glimepiride | 1 mg as a single dose | Fenofibrate 145 mg^1 once daily for 10 days | ↑1% | ↓1%
Metformin | 850 mg 3 times daily for 10 days | Fenofibrate 54 mg^1 3 times daily for 10 days | ↓9% | ↓6%
Rosiglitazone | 8 mg once daily for 5 days | Fenofibrate 145 mg^1 once daily for 14 days | ↑10% | ↑3%
Gastrointestinal agents
Omeprazole | 40 mg once daily for 5 days | Fenofibric acid delayed release capsules 135 mg as a single dose fasting | ↑6% | ↑17%
Omeprazole | 40 mg once daily for 5 days | Fenofibric acid delayed release capsules 135 mg as a single dose with food | ↑4% | ↓2%
^1 TriCor (fenofibrate) oral tablet
^2 TriCor (fenofibrate) oral micronized capsule

Table 3. Effects of Fenofibric Acid Delayed Release Capsules or Fenofibrate Co-Administration on Systemic Exposure of Other Drugs
Dosage Regimen of Fenofibric Acid Delayed Release Capsules or Fenofibrate | Dosage Regimen of Co-Administered Drug | Change in Co-Administered Drug Exposure
 |  | Analyte | AUC | Cmax
Lipid-lowering agents
Fenofibric acid delayed release capsules 135 mg once daily for 10 days | Rosuvastatin, 40 mg once daily for 10 days | Rosuvastatin | ↑6% | ↑20%
Fenofibrate 160 mg^1 once daily for 10 days | Atorvastatin, 20 mg once daily for 10 days | Atorvastatin | ↓17% | 0%
Fenofibrate 3 x 67 mg^2 as a single dose | Pravastatin, 40 mg as a single dose | Pravastatin | ↑13% | ↑13%
 |  | 3α-Hydroxyl-iso-pravastatin | ↑26% | ↑29%
Fenofibrate 160 mg^1 as a single dose | Fluvastatin, 40 mg as a single dose | (+)-3R, 5S-Fluvastatin | ↑15% | ↑16%
Fenofibrate 160 mg^1 once daily for 7 days | Simvastatin, 80 mg once daily for 7 days | Simvastatin acid | ↓36% | ↓11%
 |  | Simvastatin | ↓11% | ↓17%
 |  | Active HMG-CoA Inhibitors | ↓12% | ↓1%
 |  | Total HMG-CoA Inhibitors | ↓8% | ↓10%
Anti-diabetic agents
Fenofibrate 145 mg^1 once daily for 10 days | Glimepiride, 1 mg as a single dose | Glimepiride | ↑35% | ↑18%
Fenofibrate 54 mg^1 3 times daily for 10 days | Metformin, 850 mg 3 times daily for 10 days | Metformin | ↑3% | ↑6%
Fenofibrate 145 mg^1 once daily for 14 days | Rosiglitazone, 8 mg once daily for 5 days | Rosiglitazone | ↑6% | ↓1%
^1 TriCor (fenofibrate) oral tablet
^2 TriCor (fenofibrate) oral micronized capsule

13 NONCLINICAL TOXICOLOGY

13.1 Carcinogenesis, Mutagenesis, Impairment of Fertility

Fenofibric acid delayed release capsules

No carcinogenicity and fertility studies have been conducted with choline fenofibrate or fenofibric acid. However, because fenofibrate is rapidly converted to its active metabolite, fenofibric acid, either during or immediately following absorption both in animals and humans, studies conducted with fenofibrate are relevant for the assessment of the toxicity profile of fenofibric acid. A similar toxicity spectrum is expected after treatment with either fenofibric acid delayed release capsules or fenofibrate.

Fenofibrate

Two dietary carcinogenicity studies have been conducted in rats with fenofibrate. In the first 24-month study, Wistar rats were dosed with fenofibrate at 10, 45, and 200 mg/kg/day, approximately 0.3, 1, and 6 times the maximum recommended human dose (MRHD) of 300 mg fenofibrate daily, equivalent to 135 mg fenofibric acid delayed release capsules daily, based on body surface area comparisons. At a dose of 200 mg/kg/day (at 6 times the MRHD), the incidence of liver carcinomas was significantly increased in both sexes. A statistically significant increase in pancreatic carcinomas was observed in males at 1 and 6 times the MRHD; an increase in pancreatic adenomas and benign testicular interstitial cell tumors was observed at 6 times the MRHD in males. In a second 24-month rat carcinogenicity study in a different strain of rats (Sprague-Dawley), doses of 10 and 60 mg/kg/day (0.3 and 2 times the MRHD) produced significant increases in the incidence of pancreatic acinar adenomas in both sexes and increases in testicular interstitial cell tumors in males at 2 times the MRHD.

A 117-week carcinogenicity study was conducted in rats comparing three drugs: fenofibrate 10 and 60 mg/kg/day (0.3 and 2 times the MRHD, based on body surface area comparisons), clofibrate (400 mg/kg/day; 2 times the human dose), and gemfibrozil (250 mg/kg/day; 2 times the human dose, based on mg/m^2 surface area). Fenofibrate increased pancreatic acinar adenomas in both sexes. Clofibrate increased hepatocellular carcinoma and pancreatic acinar adenomas in males and hepatic neoplastic nodules in females. Gemfibrozil increased hepatic neoplastic nodules in males and females, while all three drugs increased testicular interstitial cell tumors in males.

In a 21-month study in CF-1 mice, fenofibrate 10, 45, and 200 mg/kg/day (approximately 0.2, 1, and 3 times the MRHD, based on body surface area comparisons) significantly increased the liver carcinomas in both sexes at 3 times the MRHD. In a second 18-month study at 10, 60, and 200 mg/kg/day, fenofibrate significantly increased the liver carcinomas in male mice and liver adenomas in female mice at 3 times the MRHD.

Electron microscopy studies have demonstrated peroxisomal proliferation following fenofibrate administration to the rat. An adequate study to test for peroxisome proliferation in humans has not been done, but changes in peroxisome morphology and numbers have been observed in humans after treatment with other members of the fibrate class when liver biopsies were compared before and after treatment in the same individual.

Fenofibrate has been demonstrated to be devoid of mutagenic potential in the following tests: Ames, mouse lymphoma, chromosomal aberration and unscheduled DNA synthesis in primary rat hepatocytes.

In fertility studies rats were given oral dietary doses of fenofibrate, males received 61 days prior to mating and females 15 days prior to mating through weaning which resulted in no adverse effect on fertility at doses up to 300 mg/kg/day (10 times the MRHD, based on body surface area comparisons).

14 CLINICAL STUDIES

14.1 Severe Hypertriglyceridemia

The effects of fenofibrate on serum triglycerides were studied in two randomized, double-blind, placebo-controlled clinical trials of 147 hypertriglyceridemic patients. Patients were treated for eight weeks under protocols that differed only in that one entered patients with baseline TG levels of 500 to 1500 mg/dL, and the other TG levels of 350 to 500 mg/dL. In patients with hypertriglyceridemia and normal cholesterolemia with or without hyperchylomicronemia, treatment with fenofibrate at dosages equivalent to 135 mg once daily of fenofibric acid delayed release capsules decreased primarily VLDL-TG and VLDL-C. Treatment of patients with elevated TG often results in an increase of LDL-C (Table 4).

Table 4. Effects of Fenofibrate in Patients With Severe Hypertriglyceridemia
Study 1 | Placebo |  |  |  | Fenofibrate
Baseline TG levels 350 to 499 mg/dL | N | Baseline Mean (mg/dL) | Endpoint Mean (mg/dL) | Mean % Change | N | Baseline Mean (mg/dL) | Endpoint Mean (mg/dL) | Mean % Change
Triglycerides | 28 | 449 | 450 | -0.5 | 27 | 432 | 223 | -46.2*
VLDL Triglycerides | 19 | 367 | 350 | 2.7 | 19 | 350 | 178 | -44.1*
Total Cholesterol | 28 | 255 | 261 | 2.8 | 27 | 252 | 227 | -9.1*
HDL Cholesterol | 28 | 35 | 36 | 4 | 27 | 34 | 40 | 19.6*
LDL Cholesterol | 28 | 120 | 129 | 12 | 27 | 128 | 137 | 14.5
VLDL Cholesterol | 27 | 99 | 99 | 5.8 | 27 | 92 | 46 | -44.7*
Study 2 | Placebo |  |  |  | Fenofibrate
Baseline TG levels 500 to 1500 mg/dL | N | Baseline Mean (mg/dL) | Endpoint Mean (mg/dL) | Mean % Change | N | Baseline Mean (mg/dL) | Endpoint Mean (mg/dL) | Mean % Change
Triglycerides | 44 | 710 | 750 | 7.2 | 48 | 726 | 308 | -54.5*
VLDL Triglycerides | 29 | 537 | 571 | 18.7 | 33 | 543 | 205 | -50.6*
Total Cholesterol | 44 | 272 | 271 | 0.4 | 48 | 261 | 223 | -13.8*
HDL Cholesterol | 44 | 27 | 28 | 5.0 | 48 | 30 | 36 | 22.9*
LDL Cholesterol | 42 | 100 | 90 | -4.2 | 45 | 103 | 131 | 45.0*
VLDL Cholesterol | 42 | 137 | 142 | 11.0 | 45 | 126 | 54 | -49.4*
* = p < 0.05 vs. Placebo

14.2 Primary Hypercholesterolemia (Heterozygous Familial and Nonfamilial) and Mixed Dyslipidemia

The effects of fenofibrate at a dose equivalent to fenofibric acid delayed release capsules 135 mg once daily were assessed from four randomized, placebo-controlled, double-blind, parallel-group studies including patients with the following mean baseline lipid values: Total-C 306.9 mg/dL; LDL-C 213.8 mg/dL; HDL-C 52.3 mg/dL; and triglycerides 191.0 mg/dL. Fenofibrate therapy lowered LDL-C, Total-C, and the LDL-C/HDL-C ratio. Fenofibrate therapy also lowered triglycerides and raised HDL-C (Table 5).

Table 5. Mean Percent Change in Lipid Parameters at End of Treatment†
Treatment Group | Total-C (mg/dL) | LDL-C (mg/dL) | HDL-C (mg/dL) | TG (mg/dL)
Pooled Cohort
Mean baseline lipid values (n = 646) | 306.9 | 213.8 | 52.3 | 191.0
All Fenofibrate (n = 361) | -18.7%* | -20.6%* | +11.0%* | -28.9%*
Placebo (n = 285) | -0.4% | -2.2% | +0.7% | +7.7%
Baseline LDL-C > 160 mg/dL and TG < 150 mg/dL
Mean baseline lipid values (n = 334) | 307.7 | 227.7 | 58.1 | 101.7
All Fenofibrate (n = 193) | -22.4%* | -31.4%* | +9.8%* | -23.5%*
Placebo (n = 141) | +0.2% | -2.2% | +2.6% | +11.7%
Baseline LDL-C > 160 mg/dL and TG ≥ 150 mg/dL
Mean baseline lipid values (n = 242) | 312.8 | 219.8 | 46.7 | 231.9
All Fenofibrate (n = 126) | -16.8%* | -20.1%* | +14.6%* | -35.9%*
Placebo (n = 116) | -3.0% | -6.6% | +2.3% | +0.9%
† Duration of study treatment was 3 to 6 months
* p = < 0.05 vs. Placebo

In a subset of the subjects, measurements of Apo B were conducted. Fenofibrate treatment significantly reduced Apo B from baseline to endpoint as compared with placebo (-25.1% vs. 2.4%, p < 0.0001, n = 213 and 143, respectively).

16 HOW SUPPLIED/STORAGE AND HANDLING

Product: 50090-4561

NDC: 50090-4561-0 90 CAPSULE, DELAYED RELEASE in a BOTTLE

17 PATIENT COUNSELING INFORMATION

Patient Counseling

Patients should be advised:

- of the potential benefits and risks of fenofibric acid delayed release capsules.
- not to use fenofibric acid delayed release capsules if there is a known hypersensitivity to fenofibrate or fenofibric acid.
- of medications that should not be taken in combination with fenofibric acid delayed release capsules.
- that if they are taking coumarin anticoagulants, fenofibric acid delayed release capsules may increase their anti-coagulant effect, and increased monitoring may be necessary.
- to continue to follow an appropriate lipid-modifying diet while taking fenofibric acid delayed release capsules.
- to take fenofibric acid delayed release capsules once daily, without regard to food, at the prescribed dose, swallowing each capsule whole.
- to return to their physician’s office for routine monitoring.
- to inform their physician of all medications, supplements, and herbal preparations they are taking and any change to their medical condition. Patients should also be advised to inform their physicians prescribing a new medication that they are taking fenofibric acid delayed release capsules.
- to inform their physician of any muscle pain, tenderness, or weakness; onset of abdominal pain; or any other new symptoms.
- not to breastfeed during treatment with fenofibric acid delayed release capsules and for 5 days after the final dose.

Manufactured by:
Fournier Laboratories Ireland Limited
Anngrove, Carrigtwohill Co. Cork, Ireland
Distributed by:
Amneal Pharmaceuticals LLC
Bridgewater, NJ 08807
03-B824 November, 2018

MEDICATION GUIDE

FENOFIBRIC ACID DELAYED RELEASE CAPSULES

Read this Medication Guide before you start taking fenofibric acid delayed release capsules and each time you get a refill. There may be new information. This information does not take the place of talking to your healthcare provider about your medical condition or your treatment.

What is the most important information I should know about fenofibric acid delayed release capsules?

Fenofibric acid delayed release capsules can cause muscle pain, tenderness or weakness, which may be symptoms of a rare but serious muscle condition called rhabdomyolysis. In some cases rhabdomyolysis can cause kidney damage and death. The risk of rhabdomyolysis may be higher when fenofibric acid delayed release capsules is given with statins. If you take a statin, tell your healthcare provider.

What are fenofibric acid delayed release capsules?

Fenofibric acid delayed release capsules are a prescription medicine used to treat cholesterol in the blood by lowering the total amount of triglycerides and LDL (bad) cholesterol, and increasing the HDL (good) cholesterol. Fenofibric acid delayed release capsules have not been shown to lower your risk of having heart problems or a stroke. You should be on a low fat and low cholesterol diet while you take fenofibric acid delayed release capsules.

The safety and effectiveness of fenofibric acid delayed release capsules in children are not known.

Who should not take fenofibric acid delayed release capsules?

Do not take fenofibric acid delayed release capsules if you:

- are allergic to fenofibric acid, or any of the ingredients in fenofibric acid delayed release capsules. See the end of this Medication Guide for a list of all the ingredients in fenofibric acid delayed release capsules.
- have severe kidney disease.
- have liver disease.
- have gallbladder disease.
- are a nursing mother.

Talk to your healthcare provider before you take fenofibric acid delayed release capsules if you have any of these conditions.

What should I tell my healthcare provider before taking fenofibric acid delayed release capsules?

Before taking fenofibric acid delayed release capsules, tell your healthcare provider about all your medical conditions, including if you:

- are allergic to any medicines.
- have ever had kidney problems.
- have ever had liver problems.
- have ever had gallbladder problems.
- are pregnant or if you plan to become pregnant. It is not known if fenofibric acid delayed release capsules will harm your unborn baby.
- are breastfeeding or plan to breastfeed. It is not known if fenofibric acid delayed release capsules pass into your breast milk. You and your healthcare provider should decide if you will take fenofibric acid delayed release capsules or breastfeed. You should not do both.

Tell your healthcare provider about all the medicines you take, including prescription and non-prescription medicines, vitamins and herbal supplements.

Using fenofibric acid delayed release capsules with certain other medicines can affect the way these medicines work and other medicines may affect how fenofibric acid delayed release capsules work. In some cases, using fenofibric acid delayed release capsules with other medicines can cause serious side effects.

Know all the medicines you take. Keep a list of them and show it to your healthcare provider when you get a new medicine.

It is especially important to tell your healthcare provider if you take any of the medicines listed below:

- anticoagulants, also known as blood thinners (warfarin, Coumadin)
- bile acid resins
- cyclosporine

Ask your healthcare provider if you are not sure if your medicine is one of these.

How should I take fenofibric acid delayed release capsules?

- You should be on a low fat and low cholesterol diet while you take fenofibric acid delayed release capsules.
- Take fenofibric acid delayed release capsules one time each day as prescribed by your healthcare provider.
- Take fenofibric acid delayed release capsules with or without food.
- Swallow fenofibric acid delayed release capsules whole. Do not break, crush, dissolve, or chew fenofibric acid delayed release capsules before swallowing. If you cannot swallow fenofibric acid delayed release capsules whole, tell your healthcare provider, you may need a different medicine.
- If you miss a dose of fenofibric acid delayed release capsules, take it as soon as you remember. If it is almost time for your next dose, just skip the missed dose. Take the next dose at your regular time. If you are not sure about your dosing, call your healthcare provider. Do not take more than one dose of fenofibric acid delayed release capsules a day unless your healthcare provider tells you to.
- If you take too much fenofibric acid delayed release capsules, contact your healthcare provider or your local emergency department.
- Do not change your dose or stop fenofibric acid delayed release capsules unless your healthcare provider tells you to.
- Your healthcare provider may do blood tests before you start taking fenofibric acid delayed release capsules and during treatment. See your healthcare provider regularly to check your cholesterol and triglyceride levels and to check for side effects.

What are the possible side effects with fenofibric acid delayed release capsules?

Fenofibric acid delayed release capsules may cause serious side effects, including:

- muscle pain, tenderness, or weakness. See "What is the most important information that I should know about fenofibric acid delayed release capsules?"
- tiredness and fever.
- abdominal pain, nausea, or vomiting. These may be signs of inflammation (swelling) of the gallbladder or pancreas.

Call your healthcare provider right away if you have any of these serious side effects.

The most common side effects with fenofibric acid delayed release capsules include:

- headache
- heartburn (indigestion)
- nausea
- muscle aches
- increases in muscle or liver enzymes that are measured by blood tests

Tell your healthcare provider if you have any side effect that bothers you or that does not go away. These are not all the possible side effects of fenofibric acid delayed release capsules. For more information, ask your healthcare provider or pharmacist.

Call your doctor for medical advice about side effects. You may report side effects to FDA at 1-800-FDA-1088.

How do I store fenofibric acid delayed release capsules?

- Store fenofibric acid delayed release capsules between 59° to 86° F (15° to 30° C).
- Protect fenofibric acid delayed release capsules from moisture.

Keep fenofibric acid delayed release capsules and all medicines out of the reach of children.

General information about the safe and effective use of fenofibric acid delayed release capsules

Medicines are sometimes prescribed for conditions that are not mentioned in the Medication Guide. Do not use fenofibric acid delayed release capsules for a condition for which it was not prescribed. Do not give fenofibric acid delayed release capsules to other people, even if they have the same condition you have. It may harm them.

This Medication Guide summarizes the most important information about fenofibric acid delayed release capsules. If you would like more information, talk to your healthcare provider. You can also ask your pharmacist or healthcare provider for information that is written for health professionals.

What are the ingredients in fenofibric acid delayed release capsules?

Active Ingredient: Fenofibric acid

Inactive Ingredients: Hypromellose, povidone, water, hydroxypropyl cellulose, colloidal silicon dioxide, sodium stearyl fumarate, methacrylic acid copolymer, talc, triethyl citrate, gelatin, titanium dioxide, and yellow iron oxide. Additionally, the 45 mg capsule shell contains black iron oxide and red iron oxide, and the 135 mg capsule shell contains FD&C Blue #2.

Manufactured for Impax Generics
Hayward, CA 94544
by Fournier Laboratories Ireland Limited
Anngrove, Carrigtwohill Co. Cork, Ireland

03-B362-R1 June, 2016

This Medication Guide has been approved by the U.S. Food and Drug Administration.

Storage

Store at 25°C (77°F); excursions permitted to 15°-30°C (59° to 86°F) [See USP controlled room temperature]. Keep out of the reach of children. Protect from moisture.